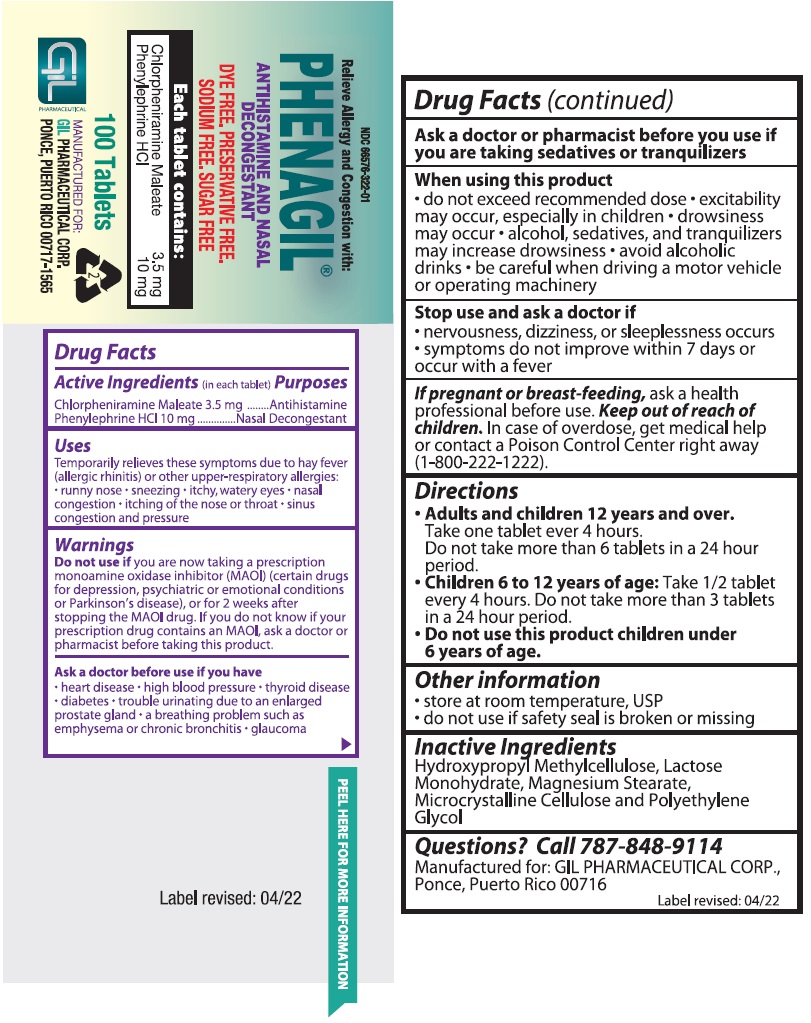 DRUG LABEL: PHENAGIL
NDC: 66576-322 | Form: TABLET
Manufacturer: Syntho Pharmaceuticals, Inc.
Category: otc | Type: HUMAN OTC DRUG LABEL
Date: 20220613

ACTIVE INGREDIENTS: CHLORPHENIRAMINE MALEATE 3.5 mg/1 1; PHENYLEPHRINE HYDROCHLORIDE 10 mg/1 1
INACTIVE INGREDIENTS: LACTOSE MONOHYDRATE; HYPROMELLOSE, UNSPECIFIED; MICROCRYSTALLINE CELLULOSE; MAGNESIUM STEARATE; POLYETHYLENE GLYCOL, UNSPECIFIED

Relieve Allergy and Congestion with:
PHENAGIL®ANTIHISTAMINE AND NASAL DECONGESTANT
DYE FREE
PRESERVATIVE FREE
SODIUM FREE
SUGAR FREE

Drug Facts

Active Ingredients (in each tablet)

Chlorpheniramine Maleate 3.5 mg

Phenylephrine HCl 10 mg

Purposes

Antihistamine

Nasal Decongestant

Uses

Temporarily relieves these symptoms due to hay fever (allergic rhinitis) or other upper-respiratory allergies:

• runny nose.

• sneezing.

• itchy, watery eyes.

• nasal congestion.

• itching of the nose or throat.

• sinus congestion and pressure.

Warnings

Do not use if you are now taking a prescription monoamine oxidase inhibitor (MAOI) (certain drugs for depression, psychiatric or emotional conditions or Parkinson’s disease), or for 2 weeks after stopping the MAOI drug. If you do not know if your prescription drug contains an MAOI, ask a doctor or pharmacist before taking this product.

Ask a doctor before use if you have

• heart disease.
• high blood pressure.
• thyroid disease.
• diabetes.
• trouble urinating due to an enlarged prostate gland.
• a breathing problem such as emphysema or chronic bronchitis.
• glaucoma.

Ask a doctor or pharmacist before you use if you are taking sedatives or tranquilizers.

When using this product

- do not exceed recommended dose.
- excitability may occur, especially in children.
- drowsiness may occur.
- alcohol, sedatives, and tranquilizers may increase drowsiness.
- avoid alcoholic drinks.
- be careful when driving a motor vehicle or operating machinery.

Stop use and ask a doctor if

.• nervousness, dizziness, or sleeplessness occurs.
• symptoms do not improve within 7 days or occur with a fever.

PREGNANCY OR BREAST FEEDING

If pregnant or breast-feeding, ask a health professional before use. Keep out of reach of children. In case of overdose, get medical help or contact a Poison Control Center right away (1-800-222-1222).

Directions

- Adults and children 12 years and over.
  Take 1 tablet every 4 hours.
  Do not take more than 6 tablets in a 24 hours.
- Children 6 to 12 years of age:: Take 1/2 tablet every 4 hours, Do not to exceed 3 tablets in a 24 hour period.
- Do not use this product children under 6 years of age.

Other information

• store at room temperature, USP.
• do not use if safety seal is broken or missing.

Inactive Ingredients

Hydroxypropyl Methylcellulose, Lactose Monohydrate, Magnesium Stearate,
Microcrystalline Cellulose and Polyethylene Glycol.

Questions? Call 787-848-9114

Manufactured for:
GIL PHARMACEUTICAL CORP.,
Ponce, Puerto Rico 00716
Manufactured by:
Syntho Pharmaceuticals, Inc.
Farmingdale, New York (NY) 11735
Label revised: 04/22

PACKAGE LABEL.PRINCIPAL DISPLAY PANEL

PHENAGIL- NDC- 66576-322-01- 100's Bottle Label.